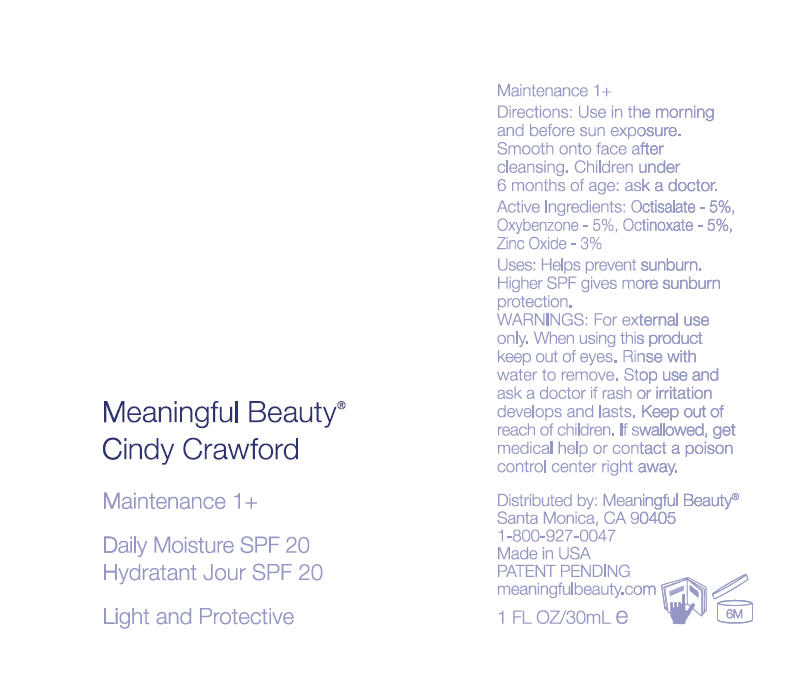 DRUG LABEL: Meaningful Beauty Cindy Crawford 
NDC: 70605-003 | Form: LOTION
Manufacturer: Guthy-Renker LLC
Category: otc | Type: HUMAN OTC DRUG LABEL
Date: 20160419

ACTIVE INGREDIENTS: OCTISALATE 5 mg/100 mL; OXYBENZONE 5 mg/100 mL; OCTINOXATE 5 mg/100 mL; ZINC OXIDE 3 mg/100 mL
INACTIVE INGREDIENTS: WATER; ALKYL (C12-15) BENZOATE; GLYCERIN; CETOSTEARYL ALCOHOL; GLYCERYL MONOSTEARATE; HYDROGENATED PALM OIL; LECITHIN, SOYBEAN; STEARETH-20; ALCOHOL; CHOLESTEROL; GLYCYRRHIZINATE DIPOTASSIUM; CAPRYLYL GLYCOL; ETHYLHEXYLGLYCERIN; HEXYLENE GLYCOL; SODIUM HYDROXIDE; CARBOMER HOMOPOLYMER TYPE A (ALLYL PENTAERYTHRITOL CROSSLINKED); EDETATE DISODIUM; PHENOXYETHANOL; BENZYL BENZOATE; BENZYL SALICYLATE; .BETA.-CITRONELLOL, (R)-; LIMONENE, (+)-; GERANIOL; BUTYLPHENYL METHYLPROPIONAL; LINALOOL, (+/-)-

Meaningful Beauty Cindy Crawford
Maintenance 1+ Daily Moisture SPF 20 UVA/UVB

Drug Facts

ACTIVE INGREDIENT

Active Ingredients | Purpose
Octisalate- 5% | Sunscreen
Oxybenzone- 5%
Octinoxate- 5%
Zinc Oxide- 3%

Uses

Helps prevent sunburn. Higher SPF gives more sunburn protection.

Directions

Apply evenly in the morning and before sun exposure and as needed. Smooth onto face after cleansing. Children under 6 months of age: ask a doctor.

Warnings

For external use only.

When using this product, keep out of eyes. Rinse with water to remove.

Stop use and ask a doctor if rash or irritation develops and lasts.

Keep out of reach of children. If swallowed, get medical help or contact a poison control center right away.

Sun Alert

Limiting sun exposure, wearing protective clothing, and using sunscreens may reduce the risks of skin aging, skin cancer, and other harmful effects of the sun.

Inactive Ingredients

Water (Aqua), C12-15 Alkyl Benzoate, Diethylhexyl 2,6-Naphthalate, Glycerin, Ascorbyl Methylsilanol Pectinate , Cetearyl Alcohol, Glyceryl Stearate, PEG-40 Stearate, Cucumis Melo (Melon) Fruit Extract, Arctostaphylos Uva Ursi Leaf Extract, Hydrogenated Palm Oil, Castor Oil Phosphate, Lecithin, Steareth-20, Alcohol Denat., Cholesterol, Magnesium Ascorbyl Phosphate, Biosaccharide Gum-1, Dipotassium Glycyrrhizate, Caprylyl Glycol, Ethylhexylglycerin, Hexylene Glycol, Triethoxycaprylylsilane, Sodium Hydroxide, Carbomer, Disodium EDTA, Phenoxyethanol, Fragrance (Parfum), Benzyl Benzoate, Benzyl Salicylate, Citronellol, Limonene, Geraniol, Hexyl Cinnamal, Butylphenyl Methylpropional, Linalool.

PRINCIPAL DISPLAY PANEL - 30mL Bottle, Pump Label

Meaningful Beauty®
Cindy Crawford

Maintenance 1+

Daily Moisture SPF 20

Light and Protective